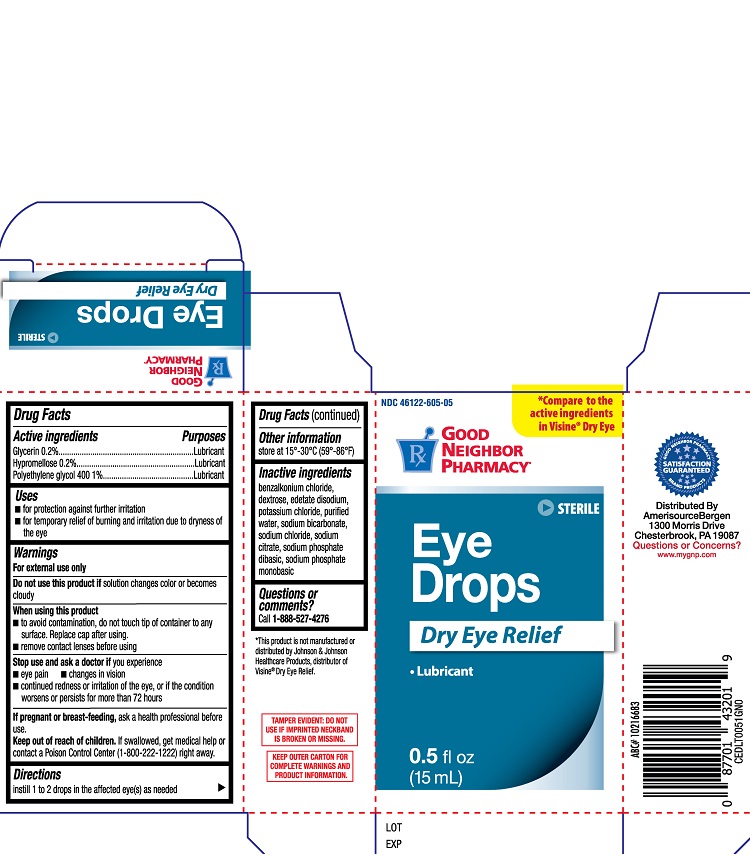 DRUG LABEL: GNP Eye Drops Dry Eye Relief
NDC: 46122-605 | Form: SOLUTION
Manufacturer: AmerisourceBergen
Category: otc | Type: HUMAN OTC DRUG LABEL
Date: 20231223

ACTIVE INGREDIENTS: GLYCERIN 0.2 g/100 mL; HYPROMELLOSES 0.2 g/100 mL; POLYETHYLENE GLYCOL 400 1 g/100 mL
INACTIVE INGREDIENTS: POTASSIUM CHLORIDE; BENZALKONIUM CHLORIDE; DEXTROSE; EDETATE DISODIUM; WATER; SODIUM CHLORIDE; SODIUM PHOSPHATE, DIBASIC; SODIUM PHOSPHATE, MONOBASIC; SODIUM BICARBONATE; SODIUM CITRATE

GNP Eye Drops Dry Eye Relief (PLD)

Active Ingredients

Glycerin .....0.2%

Hypromellose.....0.2%

Polyethylene glycol 400.....1%

Purposes

Glycerin.....Lubricant

Hypromellose.....Lubricant

Polyethylene glycol 400.....Lubricant

Uses

- for protection against further irritation
- for temporary relief of burning and irritation due to dryness of the eye

Warnings

For external use only

Do not use this product if solution changes color or becomes cloudy

When using this product

- to avoid contamination
- do not touch tip of container to any surface. Replace cap after usine
- remove contact lenses before using

Stop use and ask a doctor if you experience

- eye pain
- changes in vision
- continued redness or irritation of the eye, or if the condition worsens or persists for more than 72 hours

PREGNANCY OR BREAST FEEDING

If pregnant or breast-feeding, ask a health professional before use

Keep out of reach of children. If swallowed, get medical help or contact a Poison Control Center (1-800-222-1222) right away.

Directions

Instill 1 to 2 drops in the affected eye(s) as needed

Other informatioon

store at 15º-30ºC (59º-86ºF)

Inactive ingredients

benzalkonium chloride, dextrose, edetate disodium, potassium chloride, purified water, sodium bicarbonate, sodium chloride, sodium citrate, sodium phosphate dibasic, sodium phosphate monobasic

Questions or comments?

Call 1-800-888-527-4276